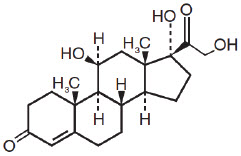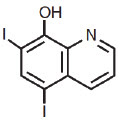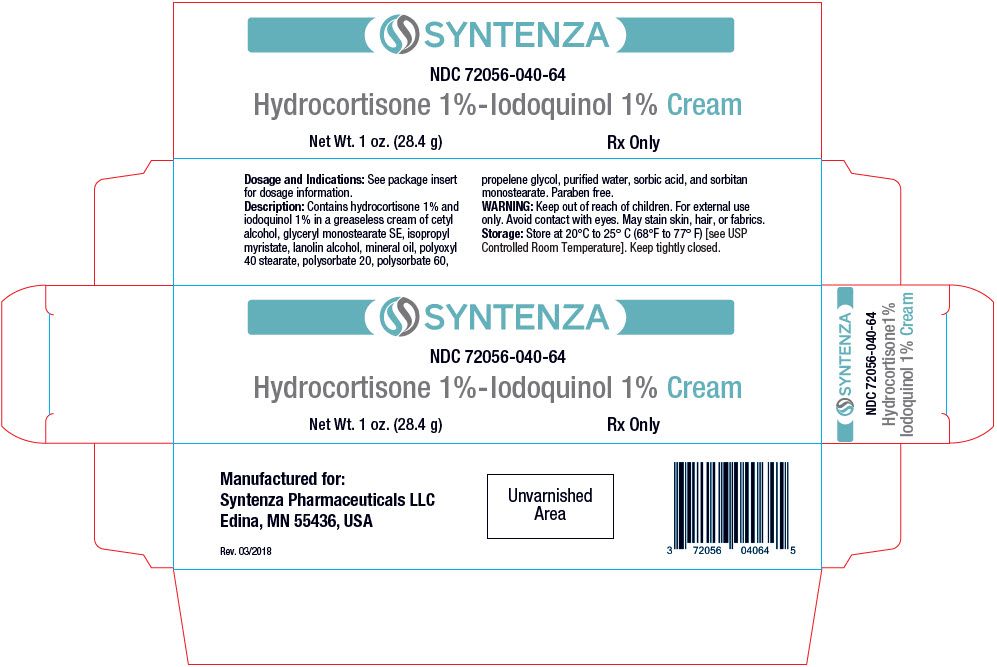 DRUG LABEL: HYDROCORTISONE IODOQUINOL
NDC: 72056-040 | Form: CREAM
Manufacturer: Syntenza Pharmaceuticals LLC
Category: prescription | Type: HUMAN PRESCRIPTION DRUG LABEL
Date: 20200506

ACTIVE INGREDIENTS: HYDROCORTISONE 10 mg/1 g; IODOQUINOL 10 mg/1 g
INACTIVE INGREDIENTS: Water; Cetyl Alcohol; Polysorbate 20

Hydrocortisone 1%-Iodoquinol 1% Cream

Rx Only

DESCRIPTION

Each gram of Hydrocortisone 1% – Iodoquinol 1% Cream contains 10 mg of hydrocortisone and 10 mg of iodoquinol in a greaseless base of cetyl alcohol, glyceryl monostearate SE, isopropyl myristate, lanolin alcohol, mineral oil, polyoxyl 40 stearate, polysorbate 20, polysorbate 60, propylene glycol, purified water, sorbic acid, and sorbitan monostearate. Paraben free.

Chemically, hydrocortisone is [Pregn-4-ene-3,20-dione, 11, 17, 21-trihydroxy-,(11ß)-] with the molecular formula C21H30O5 and is represented by the following structural formula:

and iodoquinol, 5,7-diiodo-8-quinolinol (C9H5I2NO) is represented by the following structure:

Hydrocortisone is an anti-inflammatory and antipruritic agent, while iodoquinol is an antifungal and antibacterial agent.

CLINICAL PHARMACOLOGY

Hydrocortisone has anti-inflammatory, antipruritic and vasoconstrictor properties. The mechanism of anti-inflammatory activity is unclear. There is some evidence to suggest that a recognizable correlation exists between vasoconstrictor potency and therapeutic efficacy in man.

Iodoquinol has both antifungal and antibacterial properties.

Pharmacokinetics

The extent of percutaneous absorption of topical corticosteroids is determined by many factors including the vehicle, the integrity of the epidermal barrier, and the use of occlusive dressings.

Hydrocortisone can be absorbed from normal intact skin. Inflammation and/or other inflammatory disease processes in the skin increase percutaneous absorption. Occlusive dressings substantially increase the percutaneous absorption of topical corticosteroids.

Once absorbed through the skin, hydrocortisone is metabolized in the liver and most body tissues to hydrogenated and degraded forms such as tetrahydrocortisone and tetrahydrocortisol. These are excreted in the urine, mainly conjugated as glucuronides, together with a very small proportion of unchanged hydrocortisone.

There are no data available regarding the percutaneous absorption of iodoquinol; however, following oral administration, 3-5% of the dose was recovered in the urine as a glucuronide.

INDICATIONS AND USAGE

Based on a review of a related drug by the National Research Council and subsequent FDA classification for that drug, the indications are as follows: "Possibly" Effective: Contact or atopic dermatitis; impetiginized eczema; nummular eczema; infantile eczema; endogenous chronic infectious dermatitis; stasis dermatitis; pyoderma; nuchal eczema and chronic eczematoid otitis externa; acne urticata; localized or disseminated neurodermatitis; lichen simplex chronicus; anogenital pruritus (vulvae, scroti, ani); folliculitis, bacterial dermatoses; mycotic dermatoses such as tinea (capitis, cruris, corporis, pedis); moniliasis, intertrigo. Final classification of the less-than-effective indications requires further investigation.

CONTRAINDICATIONS

Hydrocortisone 1% – Iodoquinol 1% Cream is contraindicated in those patients with a history of hypersensitivity to hydrocortisone, iodoquinol or any other components of the preparation.

WARNINGS

FOR EXTERNAL USE ONLY. Keep away from eyes. Keep out of reach of children. Keep tube tightly closed.

If irritation develops, the use of Hydrocortisone 1% – Iodoquinol 1% Cream should be discontinued and appropriate therapy instituted. Staining of the skin, hair and fabrics may occur. If extensive areas are treated or if the occlusive technique is used, the possibility exists of increased systemic absorption of the corticosteroid, and suitable precautions should be taken. Children may absorb proportionally larger amounts of topical corticosteroids and thus be more susceptible to systemic toxicity. Parents of pediatric patients should be advised not to use tight-fitting diapers or plastic pants on a child being treated in the diaper area, as these garments may constitute occlusive dressings. Iodoquinol may be absorbed through the skin and interfere with thyroid function tests. If such tests are contemplated, wait at least one month after discontinuance of therapy to perform these tests. The ferric chloride test for phenylketonuria (PKU) can yield a false positive result if iodoquinol is present in the diaper or urine.

Prolonged use may result in overgrowth of non-susceptible organisms requiring appropriate therapy.

PRECAUTIONS

Carcinogenesis, Mutagenesis, Impairment of Fertility

Long term animal studies have not been performed to evaluate the carcinogenic potential or the effect on fertility of hydrocortisone or iodoquinol.

In vitro studies to determine mutagenicity with hydrocortisone have revealed negative results. Mutagenicity studies have not been conducted with iodoquinol.

Pregnancy

Teratogenic Effects

Pregnancy Category C

Animal reproductive studies have not been conducted with Hydrocortisone 1% – Iodoquinol 1% Cream. It is not known whether Hydrocortisone 1% – Iodoquinol 1% Cream can cause fetal harm when administered to a pregnant woman or can affect reproductive capacity. Hydrocortisone 1% – Iodoquinol 1% Cream should be given to a pregnant woman only if clearly needed.

Nursing Mothers

It is not known whether this drug is excreted in human milk. Because many drugs are excreted in human milk, caution should be exercised when Hydrocortisone 1% – Iodoquinol 1% Cream is administered to a nursing woman.

Pediatric Use

Safety and effectiveness in pediatric patients below the age of 12 have not been established.

ADVERSE REACTIONS

The following local adverse reactions are reported infrequently with topical corticosteroids. These reactions are listed in an approximate decreasing order of occurrence:

 | Burning | Perioral dermatitis
 | Itching | Allergic contact dermatitis
 | Irritation | Maceration of the skin
 | Dryness | Secondary infection
 | Folliculitis | Skin atrophy
 | Hypertrichosis | Striae
 | Acneiform eruptions | Miliaria
 | Hypopigmentation

DOSAGE AND ADMINISTRATION

Apply to affected area 3 to 4 times daily in accordance with physician's directions.

HOW SUPPLIED

Hydrocortisone 1% – Iodoquinol 1% Cream is available as follows: 1 oz. tube (NDC 72056-040-64)

STORAGE

Store at 20-25°C (68-77°F) [see USP Controlled Room Temperature]. Keep tightly closed.

Manufactured for:
Syntenza Pharmaceuticals LLC
Edina, MN 55436, USA

Rev. 06/18

PRINCIPAL DISPLAY PANEL - 28.4 g Tube Carton

SYNTENZA

NDC 72056-040-64

Hydrocortisone 1%-Iodoquinol 1% Cream

Net Wt. 1 oz. (28.4 g)
Rx Only